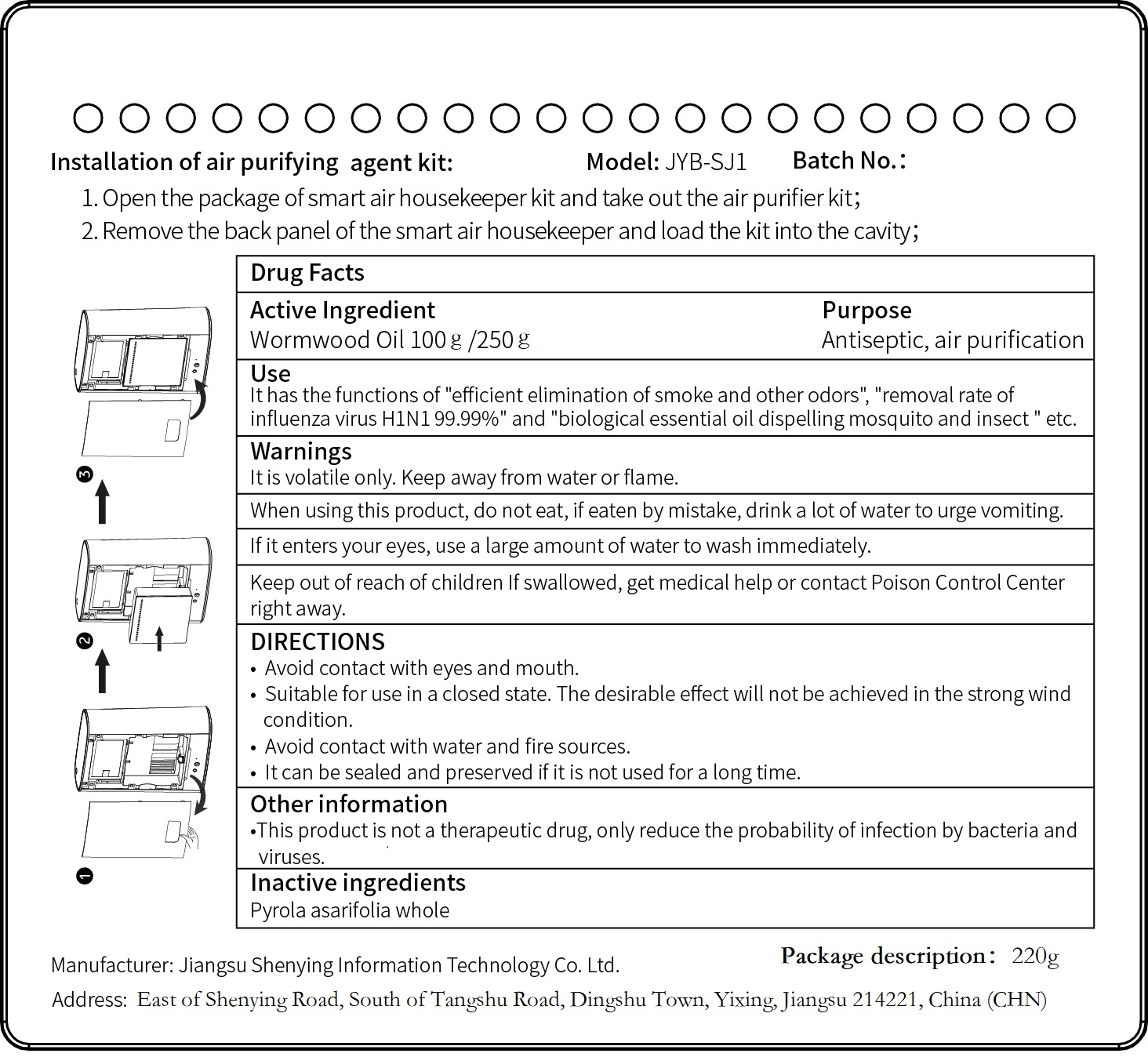 DRUG LABEL: Air Purifying Agent
NDC: 83186-002 | Form: GEL
Manufacturer: Jiangsu Shenying Information Technology Co. Ltd.
Category: otc | Type: HUMAN OTC DRUG LABEL
Date: 20201221

ACTIVE INGREDIENTS: WORMWOOD OIL 100 g/250 g
INACTIVE INGREDIENTS: PYROLA ASARIFOLIA WHOLE; EUCALYPTUS OIL; POLYSORBATE 20; LINALOOL, (+)-

Active Ingredient(s)

Wormwood Oil 100g/250g. Purpose: Antiseptic,air purification

Purpose

Antiseptic, air purification

Use

It has the functions of “efficient elimination of smoke and other odors”，“removal rete of influenza virus H1N1 99.99%" and "biological essential oil dispelling mosquito and insect“etc.

Warnings

It is volatile only. Keep away from water or flame.

When using this product,do not eat,if eaten by mistale,drink a lot of water to urge vomiting.

If it enters your eyes,use a large amount of water to wash immediately.

Keep out of reach of children if swallowed,get medical help or contact Poison Control Center right away

When using this product,do not eat, if eaten by mistake,drink a lot of water to urge vomiting

Keep out of reach of children. If swallowed, get medical help or contact a Poison Control Center right away.

Directions

- Avoid contact with eyes and mouth.
- Suitabke for use in a closed state.The desirable effect will not be achieved in the strong wind condition.
- Avoid contact with water and fire sources.
- It can be sealed and preserved if it is not used for a long time.

Other information

this product is not a therapeutic drug,only reduce the probability of infection by bacteria and viruses.

Inactive ingredients

Pyrola asarifolia whole